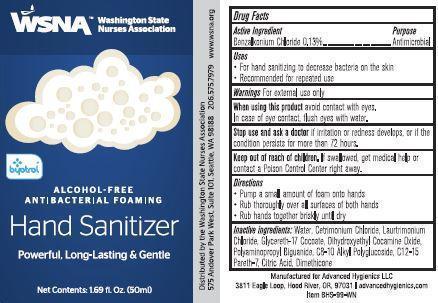 DRUG LABEL: WSNA Hand Sanitizer
                
NDC: 63002-001 | Form: LIQUID
Manufacturer: Advanced Hygienics LLC
Category: otc | Type: HUMAN OTC DRUG LABEL
Date: 20140430

ACTIVE INGREDIENTS: BENZALKONIUM CHLORIDE 1.3 mg/1 mL
INACTIVE INGREDIENTS: WATER; CETRIMONIUM CHLORIDE; LAURTRIMONIUM CHLORIDE; GLYCERETH-17 COCOATE; DIHYDROXYETHYL COCAMINE OXIDE; POLIHEXANIDE; CAPRYLYL GLUCOSIDE; C12-15 PARETH-7; CITRIC ACID MONOHYDRATE; DIMETHICONE

Drug Facts

Active Ingredient

Benzalkonium Chloride 0.13%

Purpose

Antimicrobial

Uses

For hand sanitizing to decrease bacteria on the skin

Recommended for repeated use

Warnings

For external use only

When using this product avoid contact with eyes.

In case of eye contact, flush eyes with water.

Stop use and ask a doctor if irritation or redness develops, or if the condition persists for more than 72 hours.

Keep out of reach of children.

If swallowed, get medical help or contact a Poison Control Center right away.

Directions

Pump a small amount of foam onto hands

Rub thoroughly over all surfaces of both hands

Rub hands together briskly until dry

Inactive ingredients:

Water, Cetrimonium Chloride, Laurtrimonium Chloride, Glycereth-17 Cocoate, Dihydroxyethyl Cocamine Oxide, Polyaminopropyl Biguanide, C8-10 Alkyl Polyglucoside, C12-15 Pareth-7, Citric Acid, Dimethicone

PACKAGE LABEL

WSNA

Washington State

Nurses Association

byotrol

ALCOHOL-FREE

ANTIBACTERIAL FOAMING

Hand Sanitizer

Powerful, Long-Lasting and Gentle

Net Contents: 1.69 fl. Oz. (50 ml)